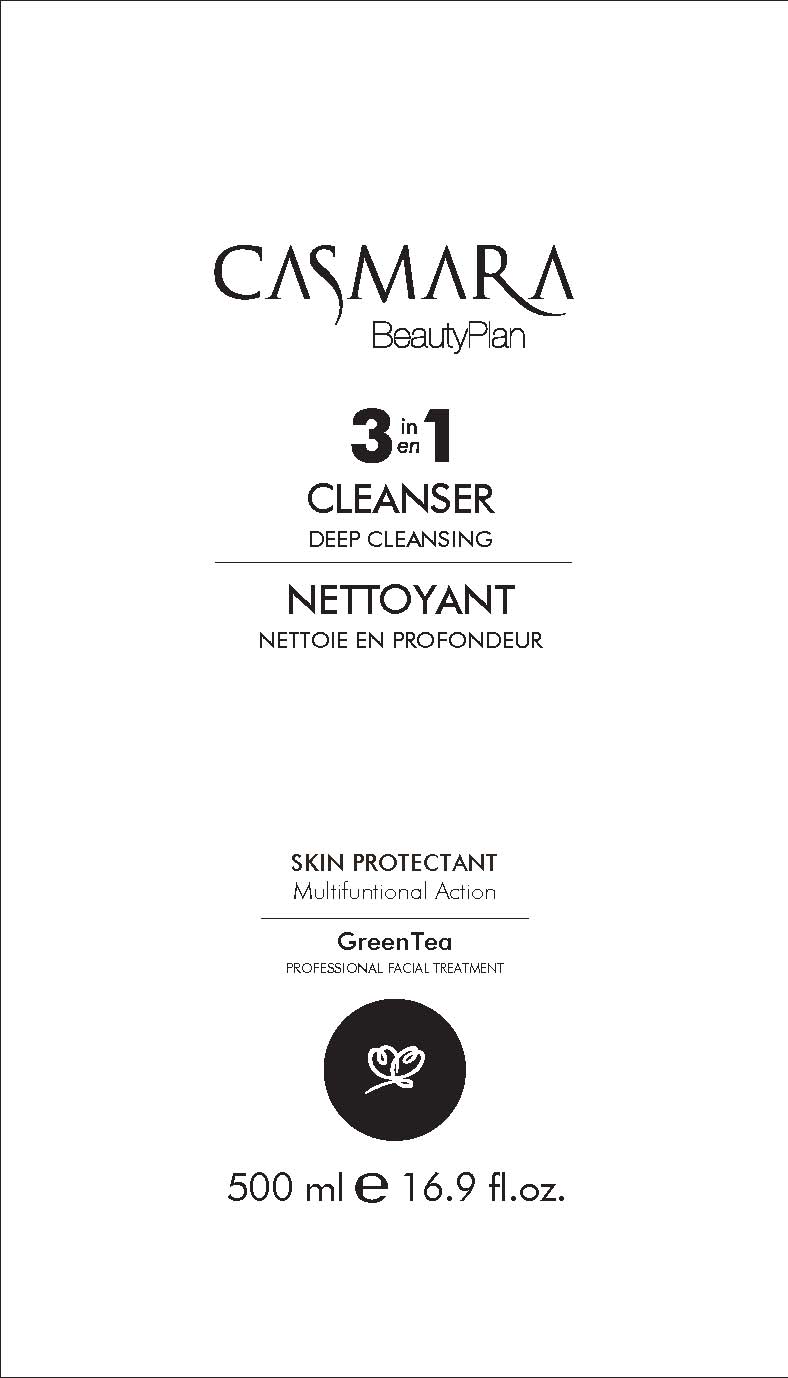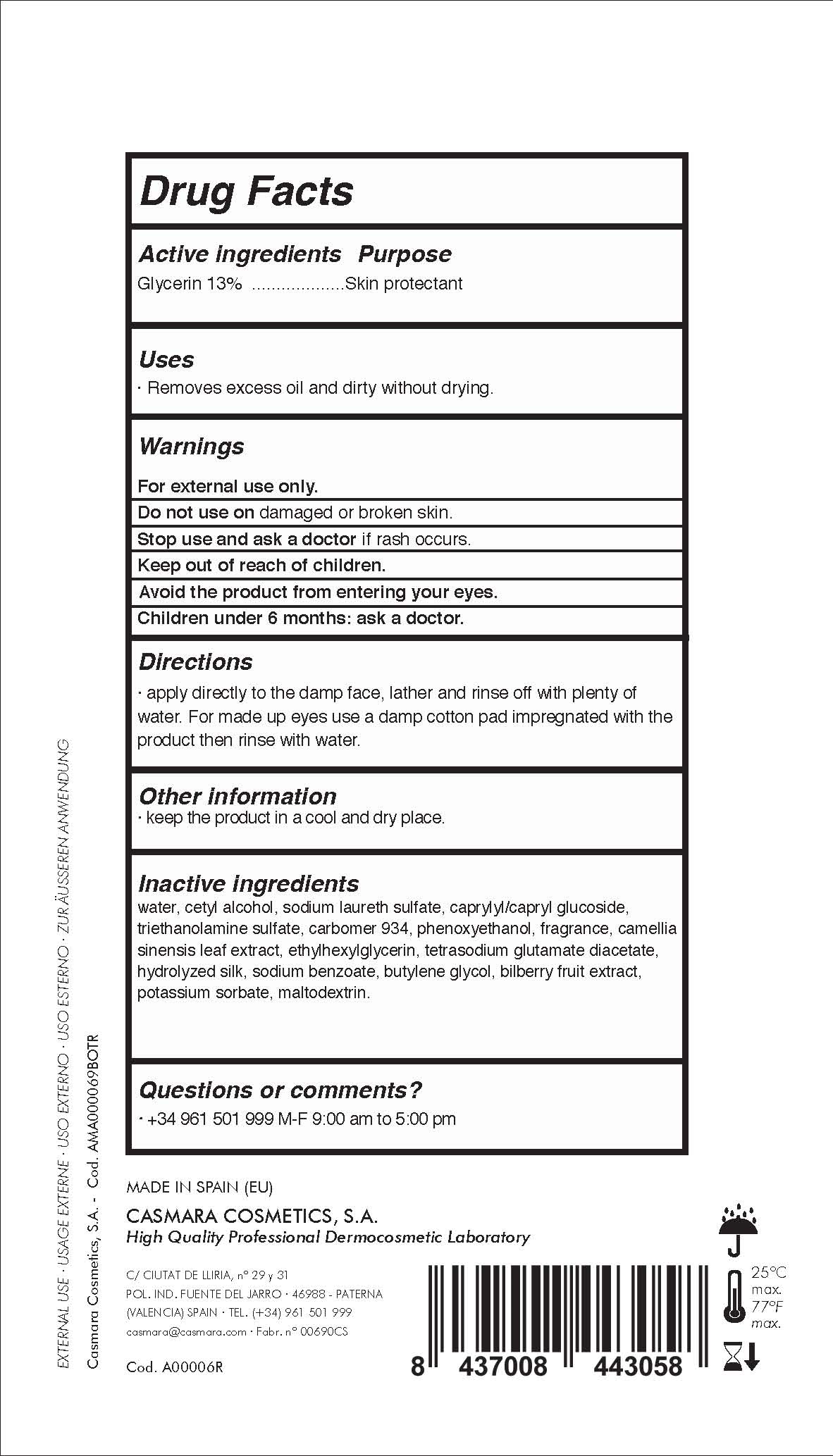 DRUG LABEL: 3 en 1 Cleanser. Deep Cleansing
NDC: 20151-075 | Form: LIQUID
Manufacturer: Casmara Cosmetics, SA
Category: otc | Type: HUMAN OTC DRUG LABEL
Date: 20161101

ACTIVE INGREDIENTS: GLYCERIN 13 mg/1 mL
INACTIVE INGREDIENTS: SODIUM LAURETH SULFATE 3.24 mg/1 mL; ETHYLHEXYLGLYCERIN 0.1 mg/1 mL; WATER 72.33 mg/1 mL; TETRASODIUM GLUTAMATE DIACETATE 0.094 mg/1 mL; PERFLUNAFENE 0.3 mg/1 mL; SODIUM BENZOATE 0.044 mg/1 mL; BILBERRY 0.0108 mg/1 mL; CAMELLIA SINENSIS FLOWER 0.28 mg/1 mL; TRIETHANOLAMINE SULFATE 1.485 mg/1 mL; CETYL ALCOHOL 4 mg/1 mL; CARBOMER 934 1.15 mg/1 mL; PHENOXYETHANOL 0.904 mg/1 mL; SILK, BASE HYDROLYZED (1000 MW) 0.044 mg/1 mL; BUTYLENE GLYCOL 0.012 mg/1 mL; POTASSIUM SORBATE 0.002 mg/1 mL; MALTODEXTRIN 0.012 mg/1 mL; CAPRYLYL GLUCOSIDE 3 mg/1 mL

3 en 1 Cleanser. Deep cleansing. Skin Protectant Multifuntional Action

WARNINGS

For external use only.

Do not use on damaged or broken skin.

Stop use and ask a doctor if rash occurs.

Keep out of reach of children.

Avoid the product from entering your eyes.

Children under 6 months: as a doctor.

Stop use and ask a doctor if rash occurs

Children under 6 months: ask a doctor

. keep out of reach of children

Questions or comments? + 34 961 501 099 M-F 9:00 am to 5:00 pm

OTHER SAFETY INFORMATION

. keep the product in a cool and dry place

Directions

. apply directly to the damp face, lather and rinse off with plenty of water.

. for made up eyes use a damp cotton pad impregnated with the product, then rinse with water

DOSAGE AND ADMINISTRATION

. apply directly to the damp face, lather and rinse off with plenty of water.

. for made up eyes use a damp cotton pad impregnated with the product, then rinse with water

Uses

. removes excess oil and dirty without drying

PURPOSE

. removes excess oil and dirty without drying.

Active Ingredients

Glycerin 13%........................... Skin Protectant

INACTIVE INGREDIENT

water, cetyl alcohol, sodium laureth sulfate, caprylyl glucoside, triethanolamine sulfate, carbomer 934, phenoxyethanol, fragrance, camellia sinensis leaf extract, ethylhexylglycerin, tetrasodium glutamate diacetate, hydrolyzed silk, sodium benzoate, butylene glycol, bilberry fruit extract, potassium sorbate, maltodextrin

PACKAGE LABEL

3 en 1 Cleanser. Deep Cleansing

Skin protectant

Multifuntional action

Green Tea

Facial Collection